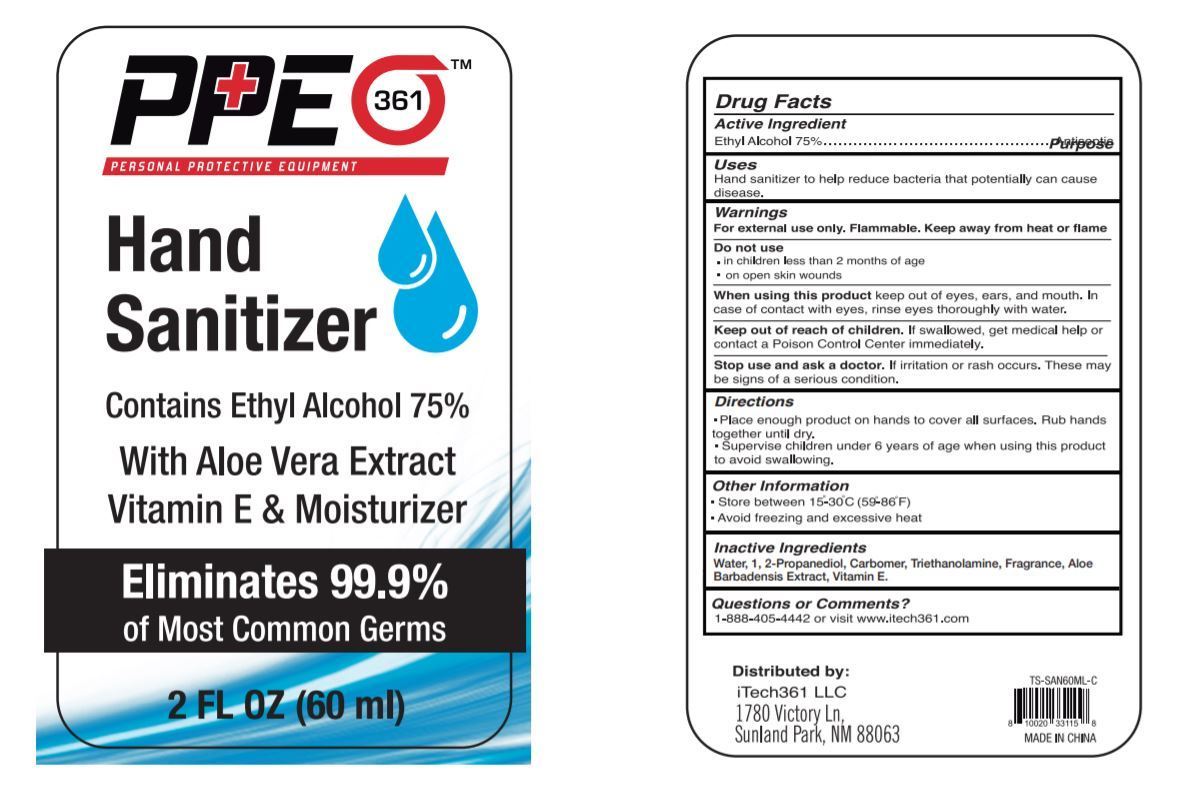 DRUG LABEL: PPE361 HAND SANITIZER WITH ALOE VERA AND VITAMIN E
NDC: 74871-063 | Form: GEL
Manufacturer: ITECH 361 LLC
Category: otc | Type: HUMAN OTC DRUG LABEL
Date: 20200925

ACTIVE INGREDIENTS: ALCOHOL 75 mL/100 mL
INACTIVE INGREDIENTS: TROLAMINE; ALOE VERA LEAF; POLYACRYLIC ACID (8000 MW); WATER; FRAGRANCE LAVENDER & CHIA F-153480; TOCOPHEROL; PROPANEDIOL

ITECH361 PPE361 HAND SANITIZER WITH ALOE VERA AND VITAMIN E 60 mL

ACTIVE INGREDIENT

Ethyl Alcohol 75%

PURPOSE

Antiseptic

USES

Hand sanitizer to help reduce bacteria that potentially can cause disease.

WARNINGS

For external use only. Flammable. Keep away from heat or flame

Do not use

■ in children less than 2 months of age

■ on open skin wounds

When using this product keep out of eyes, ears, and mouth. In case of contact with eyes, rinse eyes thoroughly with water.

Stop use and ask a doctor if irritation or rash occurs. These may be signs of a serious condition.

Keep out of reach of children. If swallowed, get medical help or contact a Poison Control Center right away.

Keep out of reach of children If swallowed get medical help or contact a Poison Control Center right away.

DIRECTIONS

■ Place enough product on hands to cover all surfaces. Rub hands together until dry.

■ Supervise children under 6 years of age when using this product to avoid swallowing.

OTHER INFORMATION

■ Store between 15-30C (59-86F)

■ Avoid freezing and excessive heat above 40C (104F)

INACTIVE INGREDIENTS

Water (Aqua), 1,2-Propanediol, Carbomer, Triethanolamine, Fragrance, Aloe Barbadensis Extract, Vitamin E.

QUESTIONS OR COMMENTS?

1-888-405-4442 or visit www.itech361.com.